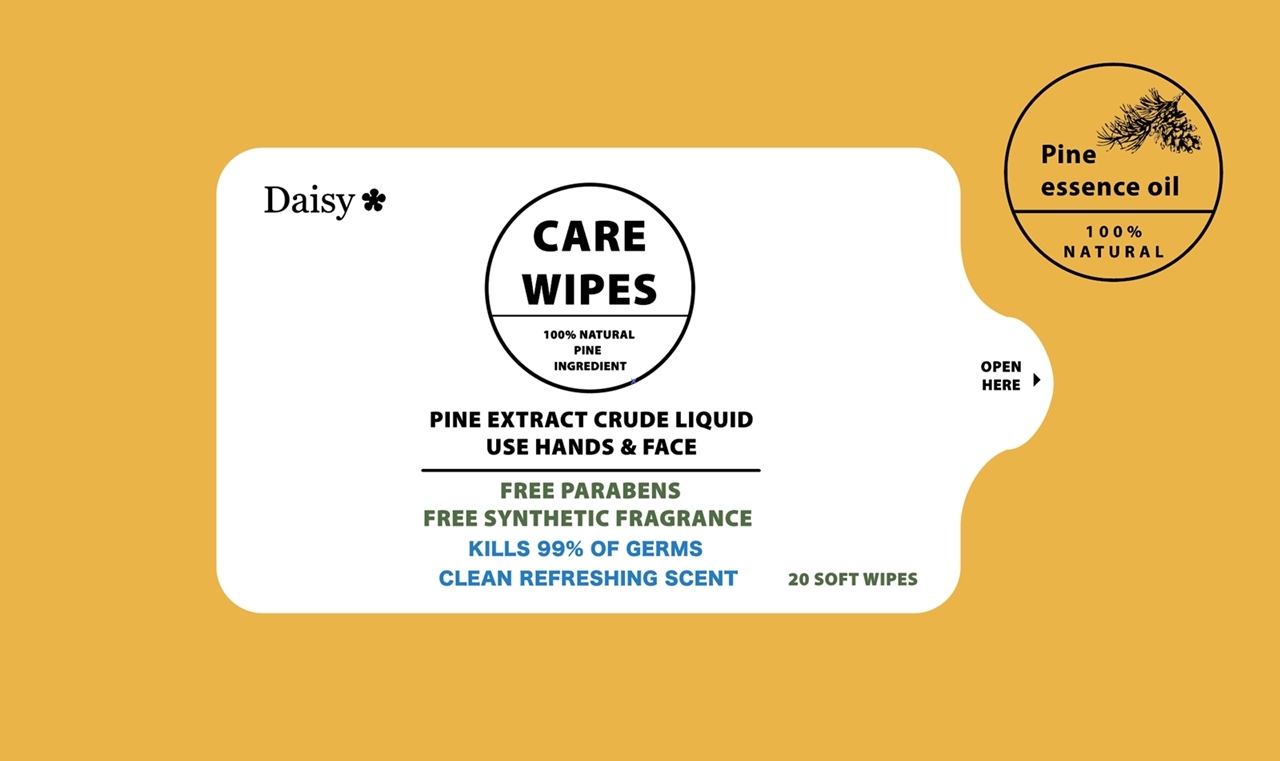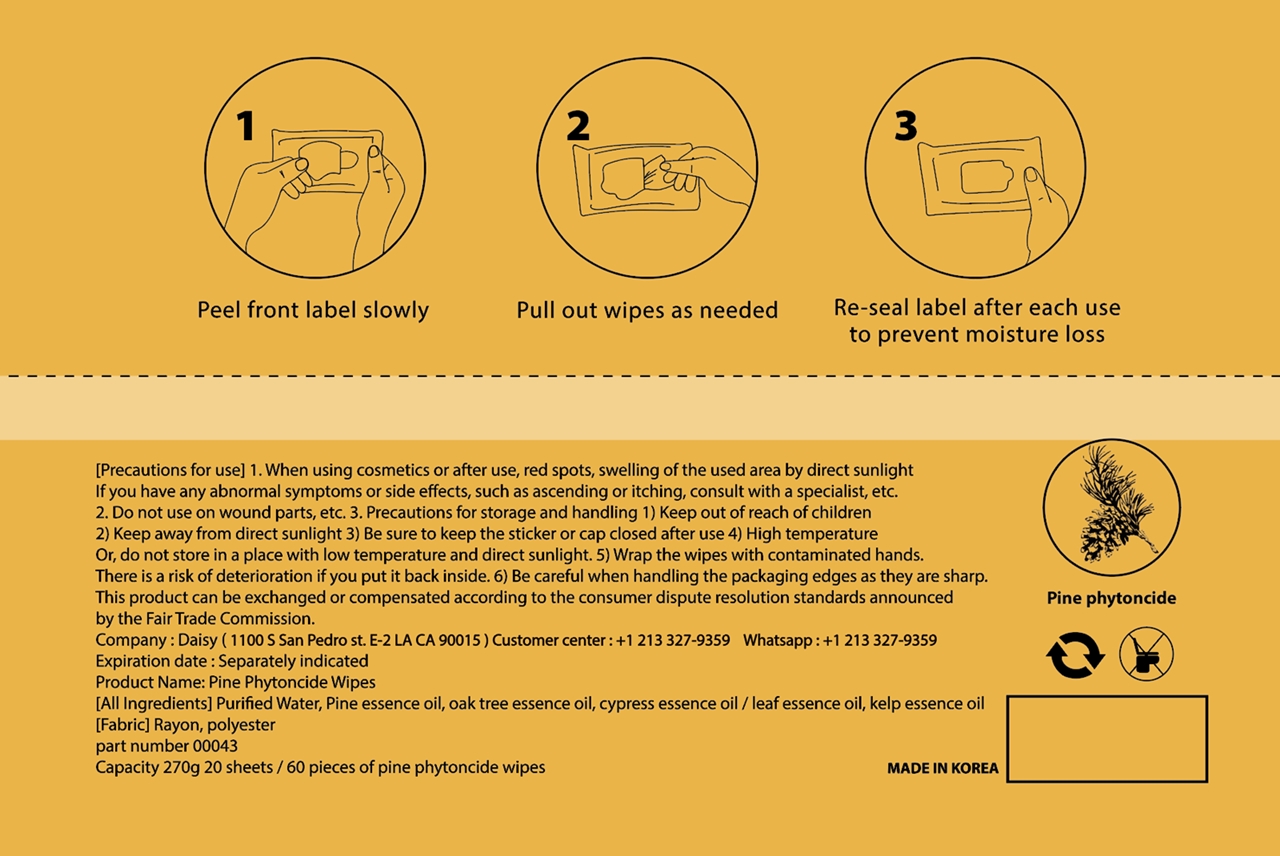 DRUG LABEL: DAISY CARE WIPES
NDC: 77748-201 | Form: LIQUID
Manufacturer: Daisy Collection
Category: otc | Type: HUMAN OTC DRUG LABEL
Date: 20200512

ACTIVE INGREDIENTS: WHITE PINE OIL 65 g/100 g
INACTIVE INGREDIENTS: CHAMAECYPARIS OBTUSA LEAF; LAMINARIA JAPONICA; ELEUTHEROCOCCUS SESSILIFLORUS WHOLE

Active Ingredient

Pine essence oil 65%

Purpose

Antiseptic

Use

1. Peel front label slowly

2. Pull out wipes as needed

3. Re-seal label after each use to prevent moisture loss

Precautions for use

1. When using cosmetics or after use, red spots, swelling of the used area by direct sunlight

If you have any abnormal symptoms or side effects, such as ascending or itching, consult with a specialist, etc.

Precautions for use

2. Do not use on wound parts, etc.

Precautions for use

3. Precautions for storage and handling

Precautions for use

1) Keep out of reach of children

Precautions for use

2) Keep away from direct sunlight

3) Be sure to keep the sticker or cap closed after use

4) High temperature Or, do not store in a place with low temperature and direct sunlight.

Precautions for use

5) Wrap the wipes with contaminated hands. There is a risk of deterioration if you put it back inside.

Precautions for use

6) Be careful when handling the packaging edges as they are sharp.

This product can be exchanged or compensated according to the consumer dispute resolution standards announced by the Fair Trade Commission.

Inactive Ingredient

Purified Water, Oak tree essence oil, Cypress essence oil / leaf essence oil, Kelp essence oil